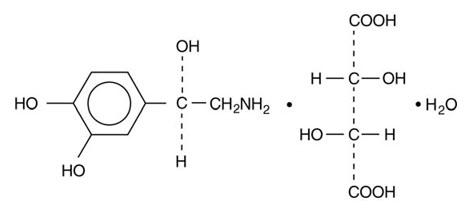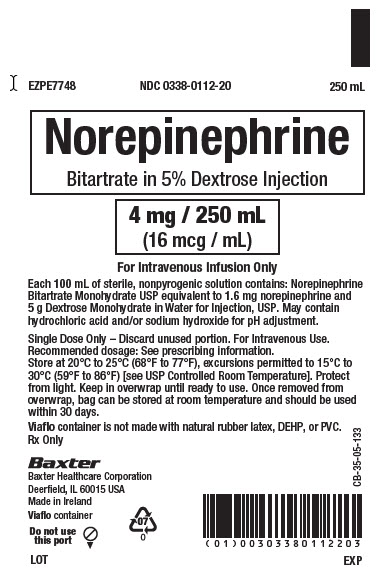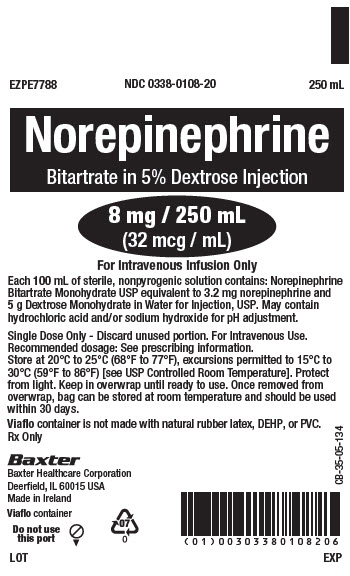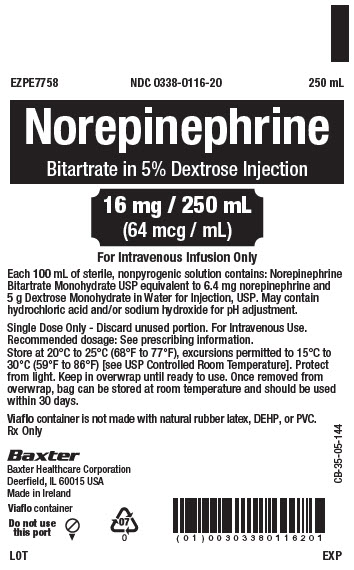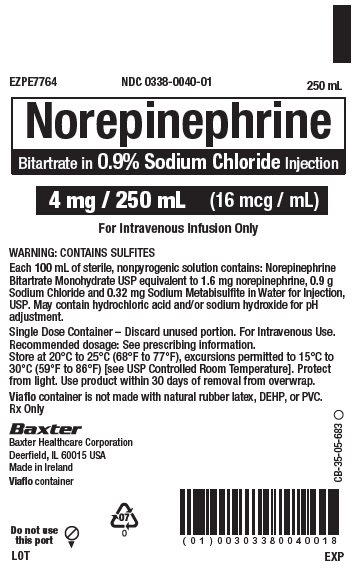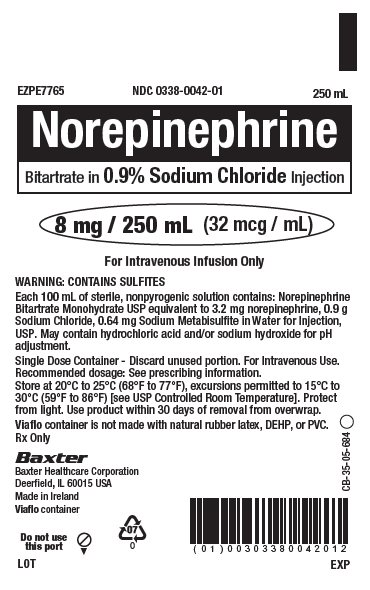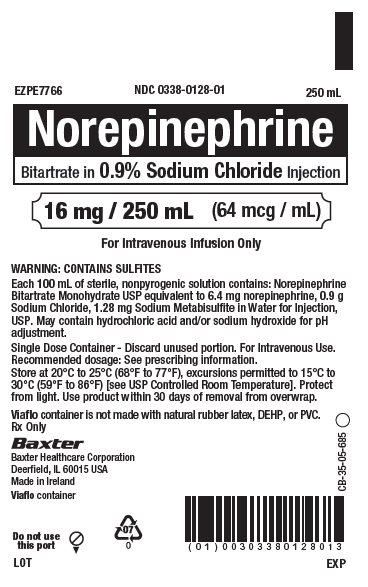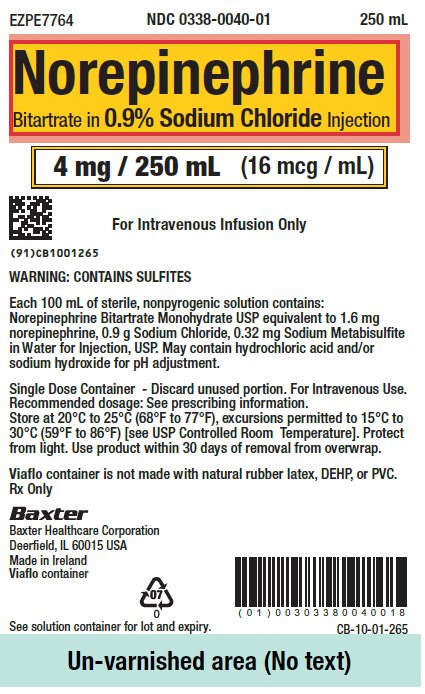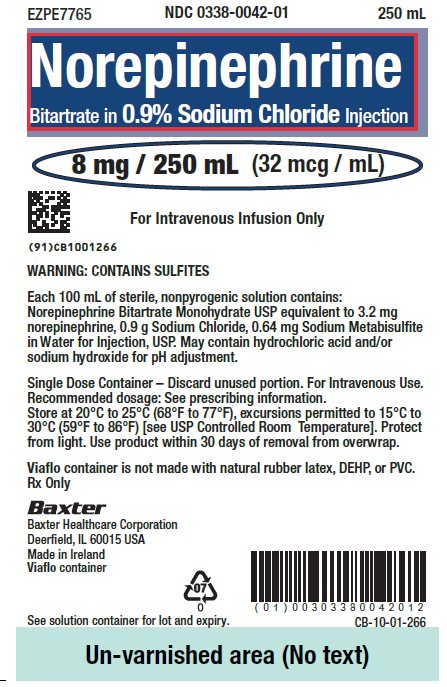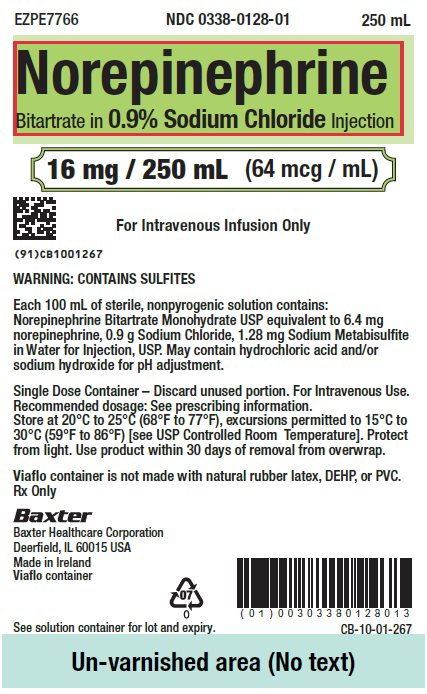 DRUG LABEL: NOREPINEPHRINE BITARTRATE
NDC: 0338-0112 | Form: INJECTION, SOLUTION
Manufacturer: Baxter Healthcare Corporation
Category: prescription | Type: HUMAN PRESCRIPTION DRUG LABEL
Date: 20260206

ACTIVE INGREDIENTS: NOREPINEPHRINE BITARTRATE 4 mg/250 mL
INACTIVE INGREDIENTS: DEXTROSE MONOHYDRATE 12.5 g/250 mL; SODIUM HYDROXIDE; HYDROCHLORIC ACID

HIGHLIGHTS OF PRESCRIBING INFORMATION

These highlights do not include all the information needed to use NOREPINEPHRINE BITARTRATE IN DEXTROSE injectionand NOREPINEPHRINE BITARTRATE IN SODIUM CHLORIDE injection safely and effectively. See full prescribing information for NOREPINEPHRINE BITARTRATE IN DEXTROSE injection and NOREPINEPHRINE BITARTRATE IN SODIUM CHLORIDE injection.
NOREPINEPHRINE BITARTRATE IN DEXTROSE injection, for intravenous use
NOREPINEPHRINE BITARTRATE IN SODIUM CHLORIDE injection, for intravenous use
Initial U.S. Approval: 1950

1 INDICATIONS AND USAGE

Norepinephrine Bitartrate in Dextrose Injection or Norepinephrine Bitartrate in Sodium Chloride Injection is a catecholamine indicated for restoration of blood pressure in adult patients with acute hypotensive states. (1)

2 DOSAGE AND ADMINISTRATION

- No further dilution prior to infusion is required. (2.1)
- Initiate at 8 mcg/min to 12 mcg/min, and adjust the rate to maintain blood pressure sufficient to maintain the circulation of vital organs. (2.2)
- The average maintenance dose ranges from 2 mcg/min to 4 mcg/min. (2.2)

3 DOSAGE FORMS AND STRENGTHS

Injection: 250-mL single dose-containers with

- 4 mg equivalent of norepinephrine (16 mcg/mL) in 5% Dextrose or 0.9% Sodium Chloride.
- 8 mg equivalent of norepinephrine (32 mcg/mL) in 5% Dextrose or 0.9% Sodium Chloride.
- 16 mg equivalent of norepinephrine (64 mcg/mL) in 5% Dextrose or 0.9% Sodium Chloride.

4 CONTRAINDICATIONS

- None. (4)

5 WARNINGS AND PRECAUTIONS

- Tissue Ischemia: Infuse Norepinephrine Bitartrate in Dextrose Injection or Norepinephrine Bitartrate in Sodium Chloride Injection into a large vein. To prevent sloughing and necrosis in areas in with extravasation, infiltrate the area with an adrenergic blocking agent in saline. (5.1)
- Hypotension After Abrupt Discontinuation: Gradually taper a norepinephrine infusion to prevent hypotension. (5.2)
- Cardiac Arrhythmias: Norepinephrine Bitartrate in Dextrose Injection or Norepinephrine Bitartrate in Sodium Chloride Injection may cause arrhythmias. Monitor cardiac function in patients with underlying heart disease. (5.3)
- Allergic Reactions with Sulfite: Norepinephrine Bitartrate in Sodium Chloride Injection contains sodium metabisulfite: Sulfite may cause allergic-type reactions. (5.4)

6 ADVERSE REACTIONS

Most common adverse reactions are hypertension, bradycardia, ischemic injury, anxiety, headache, respiratory difficulty, pulmonary edema, and extravasation necrosis at injection site. (6)

To report SUSPECTED ADVERSE REACTIONS, contact Baxter Healthcare at 1-866-888-2472 or FDA at 1-800-FDA-1088 or www.fda.gov/medwatch.

7 DRUG INTERACTIONS

- Monoamine oxidase inhibitors (MAOI) or tricyclic antidepressants of the triptyline or imipramine types may result in hypertension. (7.1, 7.2)
- Antidiabetics: Norepinephrine can decrease insulin sensitivity and raise blood glucose (7.3)
- Cyclopropane and halothane anesthetics increase cardiac autonomic irritability. (7.4)

8 USE IN SPECIFIC POPULATIONS

- Elderly patients may be at greater risk of developing adverse reactions (8.5)

FULL PRESCRIBING INFORMATION

1 INDICATIONS AND USAGE

Norepinephrine Bitartrate in Dextrose Injection or Norepinephrine Bitartrate in Sodium Chloride Injection is indicated to raise blood pressure in adult patients with severe, acute hypotension.

2 DOSAGE AND ADMINISTRATION

2.1 Important Dosage and Administration Instructions

Correct Hypovolemia

Address hypovolemia before initiation of Norepinephrine Bitartrate in Dextrose Injection or Norepinephrine Bitartrate in Sodium Chloride Injection therapy. If the patient does not respond to therapy, suspect occult hypovolemia [see Warnings and Precautions (5.1)].

Administration

Norepinephrine Bitartrate in Dextrose Injection or Norepinephrine Bitartrate in Sodium Chloride Injection is a ready to administer product that requires no further dilution prior to infusion. Parenteral drug products should be inspected visually for particulate matter and discoloration prior to administration, whenever solution and container permit. Do not use the solution if its color is pinkish or darker than slightly yellow or if it contains a precipitate.

Infuse Norepinephrine Bitartrate in Dextrose Injection or Norepinephrine Bitartrate in Sodium Chloride Injection into a large vein. Avoid infusions into the veins of the leg in the elderly or in patients with occlusive vascular disease of the legs [see Warnings and Precautions (5.1)]. Avoid using a catheter-tie-in technique.

The choice of appropriate concentration of Norepinephrine Bitartrate in Dextrose Injection or Norepinephrine Bitartrate in Sodium Chloride Injection depends on clinical fluid volume requirements. Use higher concentration solutions in patients requiring fluid restriction.

Discontinuation

When discontinuing the infusion, reduce the flow rate gradually. Avoid abrupt withdrawal.

2.2 Dosage

After an initial dosage of 8 mcg per minute to 12 mcg per minute via intravenous infusion, assess patient response and adjust dosage to maintain desired hemodynamic effect. Monitor blood pressure every two minutes until the desired hemodynamic effect is achieved, and then monitor blood pressure every five minutes for the duration of the infusion.

Typical maintenance intravenous dosage is 2 mcg per minute to 4 mcg per minute.

2.3 Drug Incompatibilities

Avoid contact with iron salts, alkalis, or oxidizing agents.

Whole blood or plasma, if indicated to increase blood volume, should be administered separately.

3 DOSAGE FORMS AND STRENGTHS

Injection: Norepinephrine bitartrate in either 5% Dextrose or 0.9% Sodium Chloride is a colorless to slightly yellow solution for intravenous infusion, supplied in 250-mL single dose containers as:

- 4 mg equivalent of norepinephrine (16 mcg/mL).
- 8 mg equivalent of norepinephrine (32 mcg/mL).
- 16 mg equivalent of norepinephrine (64 mcg/mL).

4 CONTRAINDICATIONS

None.

5 WARNINGS AND PRECAUTIONS

5.1 Tissue Ischemia

Administration of Norepinephrine Bitartrate in Dextrose Injection or Norepinephrine Bitartrate in Sodium Chloride Injection to patients who are hypotensive from hypovolemia can result in severe peripheral and visceral vasoconstriction, decreased renal perfusion and reduced urine output, tissue hypoxia, lactic acidosis, and reduced systemic blood flow despite “normal” blood pressure. Address hypovolemia prior to initiating Norepinephrine Bitartrate in Dextrose Injection or Norepinephrine Bitartrate in Sodium Chloride Injection [see Dosage and Administration (2.1)]. Avoid Norepinephrine Bitartrate in Dextrose Injection or Norepinephrine Bitartrate in Sodium Chloride Injection in patients with mesenteric or peripheral vascular thrombosis, as this may increase ischemia and extend the area of infarction.

Gangrene of the extremities has occurred in patients with occlusive or thrombotic vascular disease or who received prolonged or high dose infusions. Monitor for changes to the skin of the extremities in susceptible patients.

Extravasation of Norepinephrine Bitartrate in Dextrose Injection or Norepinephrine Bitartrate in Sodium Chloride Injection may cause necrosis and sloughing of surrounding tissue. To reduce the risk of extravasation, infuse into a large vein, check the infusion site frequently for free flow, and monitor for signs of extravasation [see Dosage and Administration (2.1)].

Emergency Treatment of Extravasation

To prevent sloughing and necrosis in areas in which extravasation has occurred, infiltrate the ischemic area as soon as possible, using a syringe with a fine hypodermic needle with 5 mg to 10 mg of phentolamine mesylate in 10 mL to 15 mL of 0.9% Sodium Chloride Injection in adults.

Sympathetic blockade with phentolamine causes immediate and conspicuous local hyperemic changes if the area is infiltrated within 12 hours.

5.2 Hypotension after Abrupt Discontinuation

Sudden cessation of the infusion rate may result in marked hypotension. When discontinuing the infusion, gradually reduce the Norepinephrine Bitartrate in Dextrose Injection or Norepinephrine Bitartrate in Sodium Chloride Injection infusion rate while expanding blood volume with intravenous fluids.

5.3 Cardiac Arrhythmias

Norepinephrine Bitartrate in Dextrose Injection or Norepinephrine Bitartrate in Sodium Chloride Injection elevates intracellular calcium concentrations and may cause arrhythmias, particularly in the setting of hypoxia or hypercarbia. Perform continuous cardiac monitoring of patients with arrhythmias.

5.4 Allergic Reactions Associated with Sulfite

This product contains sodium metabisulfite, a sulfite that may cause allergic-type reactions including anaphylactic symptoms and life-threatening or less severe asthmatic episodes in certain susceptible people. The overall prevalence of sulfite sensitivity in the general population is unknown and probably low. Sulfite sensitivity is seen more frequently in asthmatic than in non-asthmatic people.

6 ADVERSE REACTIONS

The following serious adverse reactions are described in greater detail in other sections:

- Tissue Ischemia [see Warnings and Precautions (5.1)]
- Hypotension [see Warnings and Precautions (5.2)]
- Cardiac Arrhythmias [see Warnings and Precautions (5.3)]
- Allergic Reactions associated with Sulfite [see Warnings and Precautions (5.4)]

The most common adverse reactions are hypertension and bradycardia.

The following adverse reactions can occur:

Nervous system disorders: Anxiety, headache

Respiratory disorders: Respiratory difficulty, pulmonary edema

General disorders and administration site conditions: Extravasation, injection site necrosis [see Warnings and Precautions (5.1)].

7 DRUG INTERACTIONS

7.1 MAO-Inhibiting Drugs

Co-administration of Norepinephrine Bitartrate in Dextrose Injection or Norepinephrine Bitartrate in Sodium Chloride Injection with monoamine oxidase (MAO) inhibitors or other drugs with MAO-inhibiting properties (e.g., linezolid) can cause severe, prolonged hypertension.

If administration of Norepinephrine Bitartrate in Dextrose Injection or Norepinephrine Bitartrate in Sodium Chloride Injection cannot be avoided in patients who recently have received any of these drugs and in whom, after discontinuation, MAO activity has not yet sufficiently recovered, monitor for hypertension.

7.2 Tricyclic Antidepressants

Co-administration of Norepinephrine Bitartrate in Dextrose Injection or Norepinephrine Bitartrate in Sodium Chloride Injection with tricyclic antidepressants (including amitriptyline, nortriptyline, protriptyline, clomipramine, desipramine, imipramine) can cause severe, prolonged hypertension. If administration of Norepinephrine Bitartrate in Dextrose Injection or Norepinephrine Bitartrate in Sodium Chloride Injection cannot be avoided in these patients, monitor for hypertension.

7.3 Antidiabetics

Norepinephrine Bitartrate in Dextrose Injection or Norepinephrine Bitartrate in Sodium Chloride Injection can decrease insulin sensitivity and raise blood glucose. Monitor glucose and consider dosage adjustment of antidiabetic drugs.

7.4 Halogenated Anesthetics

Concomitant use of Norepinephrine Bitartrate in Dextrose Injection or Norepinephrine Bitartrate in Sodium Chloride Injection with halogenated anesthetics (e.g., cyclopropane, desflurane, enflurane, isoflurane, and sevoflurane) may lead to ventricular tachycardia or ventricular fibrillation. Monitor cardiac rhythm in patients receiving concomitant halogenated anesthetics.

8 USE IN SPECIFIC POPULATIONS

8.1 Pregnancy

Risk Summary

Limited published data consisting of a small number of case reports and multiple small trials involving the use of norepinephrine in pregnant women at the time of delivery have not identified an increased risk of major birth defects, miscarriage or adverse maternal or fetal outcomes. There are risks to the mother and fetus from hypotension associated with septic shock, myocardial infarction and stroke which are medical emergencies in pregnancy and can be fatal if left untreated. (see Clinical Considerations). In animal reproduction studies, using high doses of intravenous norepinephrine resulted in lowered maternal placental blood flow. Clinical relevance to changes in the human fetus is unknown since the average maintenance dose is ten times lower (see Data). Increased fetal reabsorptions were observed in pregnant hamsters after receiving daily injections at approximately 2 times the maximum recommended dose on a mg/m^3 basis for four days during organogenesis (see Data).

The estimated background risk of major birth defects and miscarriage for the indicated population is unknown. All pregnancies have a background risk of birth defect, loss, or other adverse outcomes. In the U.S. general population, the estimated background risk of major birth defects and miscarriage in clinically recognized pregnancies is 2%-4% and 15%-20%, respectively.

Clinical Considerations

Disease-associated maternal and/or embryo/fetal risk

Hypotension associated with septic shock, myocardial infarction, and stroke are medical emergencies in pregnancy which can be fatal if left untreated. Delaying treatment in pregnant women with hypotension associated with septic shock, myocardial infarction and stroke may increase the risk of maternal and fetal morbidity and mortality. Life-sustaining therapy for the pregnant woman should not be withheld due to potential concerns regarding the effects of norepinephrine on the fetus.

Data

Animal Data

A study in pregnant sheep receiving high doses of intravenous norepinephrine (40 mcg/min, at approximately 10 times the average maintenance dose of 2 mcg/min -4 mcg/min in human, on a mg/kg basis) exhibited a significant decrease in maternal placental blood flow. Decreases in fetal oxygenation, urine and lung liquid flow were also observed.

Norepinephrine administration to pregnant rats on Gestation Day 16 or 17 resulted in cataract production in rat fetuses.

In hamsters, an increased number of resorptions (29.1% in study group vs. 3.4% in control group), fetal microscopic liver abnormalities and delayed skeletal ossification were observed at approximately 2 times the maximum recommended intramuscular or subcutaneous dose (on a mg/m^2 basis at a maternal subcutaneous dose of 0.5 mg/kg/day from Gestation Day 7-10).

8.2 Lactation

Risk Summary

There are no data on the presence of norepinephrine in either human or animal milk, the effects on the breastfed infant, or the effects on milk production. Clinically relevant exposure to the infant is not expected based on the short half-life and poor oral bioavailability of norepinephrine.

8.4 Pediatric Use

Safety and effectiveness in pediatric patients have not been established.

8.5 Geriatric Use

Clinical studies of norepinephrine did not include sufficient numbers of subjects aged 65 and over to determine whether they respond differently from younger subjects. Other reported clinical experience has not identified differences in responses between the elderly and younger patients. In general, dose selection for an elderly patient should be cautious, usually starting at the low end of the dosing range, reflecting the greater frequency of decreased hepatic, renal, or cardiac function, and of concomitant disease or other drug therapy.

Avoid administration of Norepinephrine Bitartrate in Dextrose Injection or Norepinephrine Bitartrate in Sodium Chloride Injection into the veins in the leg in elderly patients [see Warnings and Precautions (5.1)].

10 OVERDOSAGE

Overdosage with Norepinephrine Bitartrate in Dextrose Injection or Norepinephrine Bitartrate in Sodium Chloride Injection may result in headache, severe hypertension, reflex bradycardia, marked increase in peripheral resistance, and decreased cardiac output.

In case of overdosage, discontinue Norepinephrine Bitartrate in Dextrose Injection or Norepinephrine Bitartrate in Sodium Chloride Injection until the condition of the patient stabilizes.

11 DESCRIPTION

Norepinephrine Bitartrate in Dextrose Injection or Norepinephrine Bitartrate in Sodium Chloride Injection contains norepinephrine, a sympathomimetic amine. Norepinephrine is sometimes referred to as l-arterenol/Levarterenol or l-norepinephrine which differs from epinephrine by the absence of a methyl group on the nitrogen atom.

Chemically, norepinephrine bitartrate monohydrate is (-)-α-(aminomethyl)-3,4-dihydroxybenzyl alcohol tartrate (1:1) (salt) monohydrate and has the following structural formula:

Norepinephrine is sparingly soluble in water, very slightly soluble in alcohol and ether, and readily soluble in acids.

Norepinephrine Bitartrate in 5% Dextrose Injection is supplied as a sterile aqueous solution administered by intravenous infusion. Each mL contains the equivalent of 16 mcg, 32 mcg, or 64 micrograms of norepinephrine base supplied as 31.9 mcg, 63.8 mcg, and 127.6 micrograms per mL of norepinephrine bitartrate monohydrate. It contains dextrose monohydrate (50 mg/mL) and may contain hydrochloric acid and/or sodium hydroxide for pH adjustment. It has a target pH of 3.7. The air in the containers has been displaced by nitrogen gas.

Norepinephrine Bitartrate in 0.9% Sodium Chloride Injection is supplied as a sterile aqueous solution administered by intravenous infusion. Each mL contains the equivalent of 16 mcg, 32 mcg, or 64 micrograms of norepinephrine base supplied as 31.9 mcg, 63.8 mcg, and 127.6 micrograms per mL of norepinephrine bitartrate monohydrate. It contains sodium chloride (9 mg/mL), sodium metabisulfite (3.2 mcg/mL, 6.4 mcg/mL and 12.8 mcg/mL, respectively) and may contain hydrochloric acid and/or sodium hydroxide for pH adjustment. It has a target pH of 3.8. The air in the containers has been displaced by nitrogen gas.

12 CLINICAL PHARMACOLOGY

12.1 Mechanism of Action

Norepinephrine is a peripheral vasoconstrictor (alpha-adrenergic action) and an inotropic stimulator of the heart and dilator of coronary arteries (beta-adrenergic action).

12.2 Pharmacodynamics

The primary pharmacodynamic effects of norepinephrine are cardiac stimulation and vasoconstriction. Cardiac output is generally unaffected, although it can be decreased, and total peripheral resistance is also elevated. The elevation in resistance and pressure result in reflex vagal activity, which slows the heart rate and increases stroke volume. The elevation in vascular tone or resistance reduces blood flow to the major abdominal organs as well as to skeletal muscle. Coronary blood flow is substantially increased secondary to the indirect effects of alpha stimulation. After intravenous administration, a pressor response occurs rapidly and reaches steady state within 5 minutes. The pharmacologic actions of norepinephrine are terminated primarily by uptake and metabolism in sympathetic nerve endings. The pressor action stops within 1 minutes-2 minutes after the infusion is discontinued.

12.3 Pharmacokinetics

Absorption

Following initiation of intravenous infusion, the steady state plasma concentration is achieved in 5 min.

Distribution

Plasma protein binding of norepinephrine is approximately 25%. It is mainly bound to plasma albumin and to a smaller extent to prealbumin and alpha 1-acid glycoprotein. The volume of distribution is 8.8 L. Norepinephrine localizes mainly in sympathetic nervous tissue. It crosses the placenta but not the blood-brain barrier.

Elimination

The mean half-life of norepinephrine is approximately 2.4 min. The average metabolic clearance is 3.1 L/min.

Metabolism

Norepinephrine is metabolized in the liver and other tissues by a combination of reactions involving the enzymes catechol-O-methyltransferase (COMT) and monoamine oxidase (MAO). The major metabolites are normetanephrine and 3-methoxy-4-hydroxy mandelic acid (vanillylmandelic acid, VMA), both of which are inactive. Other inactive metabolites include 3-methoxy-4-hydroxyphenylglycol, 3,4-dihydroxymandelic acid, and 3,4-dihydroxyphenylglycol.

Excretion

Norepinephrine metabolites are excreted in urine primarily as the sulfate conjugates and, to a lesser extent, as the glucuronide conjugates. Only small quantities of norepinephrine are excreted unchanged.

13 NONCLINICAL TOXICOLOGY

13.1 Carcinogenesis, Mutagenesis, Impairment of Fertility

Carcinogenesis, mutagenesis, and fertility studies have not been performed.

16 HOW SUPPLIED/STORAGE AND HANDLING

Norepinephrine Bitartrate in Dextrose Injection or Norepinephrine Bitartrate in Sodium Chloride Injection for intravenous infusion is a colorless to slightly yellow solution available in single-dose, ready-to-use containers in an amber/foil overwrap. Each 250 mL of Norepinephrine Bitartrate in Dextrose Injection or Norepinephrine Bitartrate in Sodium Chloride Injection , 4 mg/250 mL, 8 mg/250 mL, and 16 mg/250 mL contains the equivalent of 4 mg, 8 mg, and 16 mg of norepinephrine, respectively (provided as norepinephrine bitartrate monohydrate). Norepinephrine Bitartrate in Dextrose Injection or Norepinephrine Bitartrate in Sodium Chloride Injection is available in the following:

Norepinephrine Bitartrate in 5% Dextrose Injection
Product Description | NDC Number
Twenty containers of 4 mg/250 mL (16 mcg/mL) | NDC 0338-0112-20
Twenty containers of 8 mg/250 mL (32 mcg/mL) | NDC 0338-0108-20
Twenty containers of 16 mg/250 mL (64 mcg/mL) | NDC 0338-0116-20

Norepinephrine Bitartrate in 0.9% Sodium Chloride Injection
Product Description | NDC Number
Twenty containers of 4 mg/250 mL (16 mcg/mL) | NDC 0338-0040-20
Twenty containers of 8 mg/250 mL (32 mcg/mL) | NDC 0338-0042-20
Twenty containers of 16 mg/250 mL (64 mcg/mL) | NDC 0338-0128-20

Store at room temperature [20°C to 25°C (68°F to 77°F)], excursions permitted to 15°C to 30°C (59°F to 86°F) [see USP Controlled Room Temperature]. Protect from light. Once the overwrap is removed, the bag can be stored at room temperature for up to 30 days.

17 PATIENT COUNSELING INFORMATION

Risk of Tissue Damage

Advise the patient, family, or caregiver to report signs of extravasation urgently [see Warnings and Precautions (5.1)].

Manufactured by:
Baxter Healthcare Corporation
Deerfield, IL 60015 USA

Made in Ireland

Baxter and Viaflo are trademarks of Baxter International, Inc. or its subsidiaries.

CB-30-03-122

PACKAGE/LABEL PRINCIPAL DISPLAY PANEL

Container Label

EZPE7748
NDC 0338-0112-20

250 mL

Norepinephrine
Bitartrate in 5% Dextrose Injection

4 mg / 250 mL
(16 mg / mL)
For Intravenous Infusion Only

Each 100mL of sterile, nonpyrogenic solution contains: Norepinephrine
Bitartrate Monohydrate USP equivalent to 1.6 mg norepinephrine and
5 g Dextrose Monohydrate in Water for Injection, USP. May contain
hydrochloric acid and/or sodium hydroxide for pH adjustment.

Single Dose Only – Discard unused portion. For Intravenous Use.
Recommended dosage: See prescribing information.
Store at 20°C to 25°C (68°F to 77°F), excursions permitted to 15° C to
30°C (59°F to 86° F) [see USP Controlled Room Temperature.] Protect
from light. Keep in overwrap until ready to use. Once removed from
overwrap, bag can be stored at room temperature and should be used
within 30 days.

VIAFLO container is not made with natural rubber latex, DEHP, or PVC.
Rx Only

Baxter Logo
Baxter Healthcare Corporation
Deerfield, IL 60015 USA
Made in Ireland

CB-35-05-133

VIAFLO container

Symbol
07
0

Symbol
Do not use
this port

Barcode
(01)00303380112203

LOT

EXP

Container Label

EZPE7788
NDC 0338-0108-20
250 mL

Norepinephrine
Bitartrate in 5% Dextrose Injection

8 mg / 250 mL
(32 mcg / mL)
For Intravenous Infusion Only

Each 100 mL of sterile, nonpyrogenic solution contains: Norepinephrine
Bitartrate Monohydrate USP equivalent to 3.2 mg norepinephrine and
5 g Dextrose Monohydrate in Water for Injection, USP. May contain
hydrochloric acid and/or sodium hydroxide for pH adjustment.

Single Dose Only – Discard unused portion. For Intravenous Use.
Recommended dosage: See prescribing information.
Store at 20°C to 25°C (68°F to 77°F), excursions permitted to 15°C to
30°C (59°F to 86°F). [See USP Controlled Room Temperature.] Protect
from light. Keep in overwrap until ready to use. Once removed from
overwrap, bag can be stored at room temperature and should be used
within 30 days.

VIAFLO container is not made with natural rubber latex, DEHP, or PVC.
Rx Only

Baxter Logo
Baxter Healthcare Corporation
Deerfield, IL 60015 USA
Made in Ireland

VIAFLO container

Symbol
Do not use
this port

Symbol
07
0

CB-35-05-134
Symbol
1

Barcode
(01)00303380108206

LOT

EXP

Container Label

EZPE7758
NDC 0338-0116-20
250 mL

Norepinephrine
Bitartrate in 5% Dextrose Injection

16 mg / 250 mL
(64 mcg / mL)
For Intravenous Infusion Only

Each 100 mL of sterile, nonpyrogenic solution contains: Norepinephrine
Bitartrate Monohydrate USP equivalent to 6.4 mg norepinephrine and
5 g Dextrose Monohydrate in Water for Injection, USP. May contain
hydrochloric acid and/or sodium hydroxide for pH adjustment.

Single Dose Only – Discard unused portion. For Intravenous Use.
Recommended dosage: See prescribing information.
Store at 20°C to 25°C (68°F to 77°F), excursions permitted to 15°C to
30°C (59°F to 86°F). [See USP Controlled Room Temperature.] Protect
from light. Keep in overwrap until ready to use. Once removed from
overwrap, bag can be stored at room temperature and should be used
within 30 days.

VIAFLO container is not made with natural rubber latex, DEHP, or PVC.
Rx Only

Baxter Logo
Baxter Healthcare Corporation
Deerfield, IL 60015 USA
Made in Ireland

VIAFLO container

Symbol
Do not use
this port

Symbol
07
0

CB-35-05-144
Symbol
1

Barcode
(01)00303380116201

LOT

EXP

Container Label

EZPE7764
NDC 0338-0040-01
250 mL

Norepinephrine
Bitartrate in 0.9% Sodium Chloride Injection

4 mg / 250 mL (16 mcg / mL)
For Intravenous Infusion Only

WARNING: CONTAINS SULFITES
Each 100 mL of sterile, nonpyrogenic solution contains: Norepinephrine
Bitartrate Monohydrate USP equivalent to 1.6 mg norepinephrine, 0.9 g
Sodium Chloride and 0.32 mg Sodium Metabisulfate in Water for Injection,
USP. May contain hydrochloric acid and/or sodium hydroxide for pH
adjustment.

Single Dose Only – Discard unused portion. For Intravenous Use.
Recommended dosage: See prescribing information.
Store at 20°C to 25°C (68°F to 77°F), excursions permitted to 15°C to
30°C (59°F to 86°F) [see USP Controlled Room Temperature]. Protect
from light. Use product within 30 days of removal from overwrap.
Viaflo container is not made with natural rubber latex, DEHP, or PVC.
Rx Only

Baxter Logo
Baxter Healthcare Corporation
Deerfield, IL 60015 USA
Made in Ireland
Viaflo container

Do not use
this port
Symbol

Symbol
07
0

Barcode
(01)00303380040018

CB-35-05-683

LOT

EXP

Container Label

EZPE7765
NDC 0338-0042-01
250 mL

Norepinephrine
Bitartrate in 0.9% Sodium Chloride Injection

8 mg / 250 mL (32 mcg / mL)
For Intravenous Infusion Only

WARNING: CONTAINS SULFITES
Each 100 mL of sterile, nonpyrogenic solution contains: Norepinephrine
Bitartrate Monohydrate USP equivalent to 3.2 mg norepinephrine, 0.9 g
Sodium Chloride, 0.64 mg Sodium Metabisulfate in Water for Injection,
USP. May contain hydrochloric acid and/or sodium hydroxide for pH
adjustment.

Single Dose Only – Discard unused portion. For Intravenous Use.
Recommended dosage: See prescribing information.
Store at 20°C to 25°C (68°F to 77°F), excursions permitted to 15°C to
30°C (59°F to 86°F) [see USP Controlled Room Temperature]. Protect
from light. Use product within 30 days of removal from overwrap.
Viaflo container is not made with natural rubber latex, DEHP, or PVC.
Rx Only

Baxter Logo
Baxter Healthcare Corporation
Deerfield, IL 60015 USA
Made in Ireland
Viaflo container

Do not use
this port
Symbol

Symbol
07
0

CB-35-05-684

Barcode
(01)00303380042012

LOT

EXP

Container Label

EZPE7766
NDC 0338-0128-01
250 mL

Norepinephrine
Bitartrate in 0.9% Sodium Chloride Injection

16 mg / 250 mL (64 mcg / mL)
For Intravenous Infusion Only

WARNING: CONTAINS SULFITES
Each 100 mL of sterile, nonpyrogenic solution contains: Norepinephrine
Bitartrate Monohydrate USP equivalent to 6.4 mg norepinephrine, 0.9 g
Sodium Chloride, 1.28 mg Sodium Metabisulfate in Water for Injection,
USP. May contain hydrochloric acid and/or sodium hydroxide for pH
adjustment.

Single Dose Only – Discard unused portion. For Intravenous Use.
Recommended dosage: See prescribing information.
Store at 20°C to 25°C (68°F to 77°F), excursions permitted to 15°C to
30°C (59°F to 86°F) [see USP Controlled Room Temperature]. Protect
from light. Use product within 30 days of removal from overwrap.

Viaflo container is not made with natural rubber latex, DEHP, or PVC.
Rx Only

Baxter Logo
Baxter Healthcare Corporation
Deerfield, IL 60015 USA
Made in Ireland
Viaflo container

Do not use
this port
Symbol

Symbol
07
0

CB-35-05-685

Barcode
(01)003033800128013

LOT

EXP

Overwrap Label

EZPE7764
NDC 0338-0040-01
250 mL

Norepinephrine
Bitartrate in 0.9% Sodium Chloride Injection

4 mg / 250 mL (16 mcg / mL)

QR code

For Intravenous Infusion Only

(91)CB1001265

WARNING: CONTAINS SULFITES

Each 100 mL of sterile, nonpyrogenic solution contains:
Norepinephrine Bitartrate Monohydrate USP equivalent to 1.6 mg
norepinephrine, 0.9 g Sodium Chloride, 0.32 mg Sodium Metabisulfate
in Water for Injection, USP. May contain hydrochloric acid and/or
sodium hydroxide for pH adjustment.

Single Dose Only – Discard unused portion. For Intravenous Use.
Recommended dosage: See prescribing information.
Store at 20°C to 25°C (68°F to 77°F), excursions permitted to 15°C to
30°C (59°F to 86°F) [see USP Controlled Room Temperature]. Protect
from light. Use within 30 days of removal from overwrap.

Viaflo container is not made with natural rubber latex, DEHP, or PVC.
Rx Only

Baxter Logo
Baxter Healthcare Corporation
Deerfield, IL 60015 USA
Made in Ireland
Viaflo container

Symbol
07
0

Barcode
(01)00303380040018

See solution container for lot and expiry.

CB-10-01-265

Un-varnished area (No text)

Overwrap Label

EZPE7765
NDC 0338-0042-01
250 mL

Norepinephrine
Bitartrate in 0.9% Sodium Chloride Injection

8 mg / 250 mL (32 mcg / mL)

QR code

For Intravenous Infusion Only

(91)CB1001266

WARNING: CONTAINS SULFITES

Each 100 mL of sterile, nonpyrogenic solution contains:
Norepinephrine Bitartrate Monohydrate USP equivalent to 3.2 mg
norepinephrine, 0.9 g Sodium Chloride, 0.64 mg Sodium Metabisulfate
in Water for Injection, USP. May contain hydrochloric acid and/or
sodium hydroxide for pH adjustment.

Single Dose Only – Discard unused portion. For Intravenous Use.
Recommended dosage: See prescribing information.
Store at 20°C to 25°C (68°F to 77°F), excursions permitted to 15°C to
30°C (59°F to 86°F) [see USP Controlled Room Temperature]. Protect
from light. Use within 30 days of removal from overwrap.

Viaflo container is not made with natural rubber latex, DEHP, or PVC.
Rx Only

Baxter Logo
Baxter Healthcare Corporation
Deerfield, IL 60015 USA
Made in Ireland
Viaflo container

Symbol
07
0

Barcode
(01)00303380042012

See solution container for lot and expiry.

CB-10-01-266

Un-varnished area (No text)

Overwrap Label

EZPE7766
NDC 0338-0128-01
250 mL

Norepinephrine
Bitartrate in 0.9% Sodium Chloride Injection

16 mg / 250 mL (64 mcg / mL)

QR code

For Intravenous Infusion Only

(91)CB1001267

WARNING: CONTAINS SULFITES

Each 100 mL of sterile, nonpyrogenic solution contains:
Norepinephrine Bitartrate Monohydrate USP equivalent to 6.4 mg
norepinephrine, 0.9 g Sodium Chloride, 1.28 mg Sodium Metabisulfate
in Water for Injection, USP. May contain hydrochloric acid and/or
sodium hydroxide for pH adjustment.

Single Dose Only – Discard unused portion. For Intravenous Use.
Recommended dosage: See prescribing information.
Store at 20°C to 25°C (68°F to 77°F), excursions permitted to 15°C to
30°C (59°F to 86°F) [see USP Controlled Room Temperature]. Protect
from light. Use within 30 days of removal from overwrap.

Viaflo container is not made with natural rubber latex, DEHP, or PVC.
Rx Only

Baxter Logo
Baxter Healthcare Corporation
Deerfield, IL 60015 USA
Made in Ireland
Viaflo container

Symbol
07
0

Barcode
(01)00303380128013

See solution container for lot and expiry.

CB-10-01-267

Un-varnished area (No text)